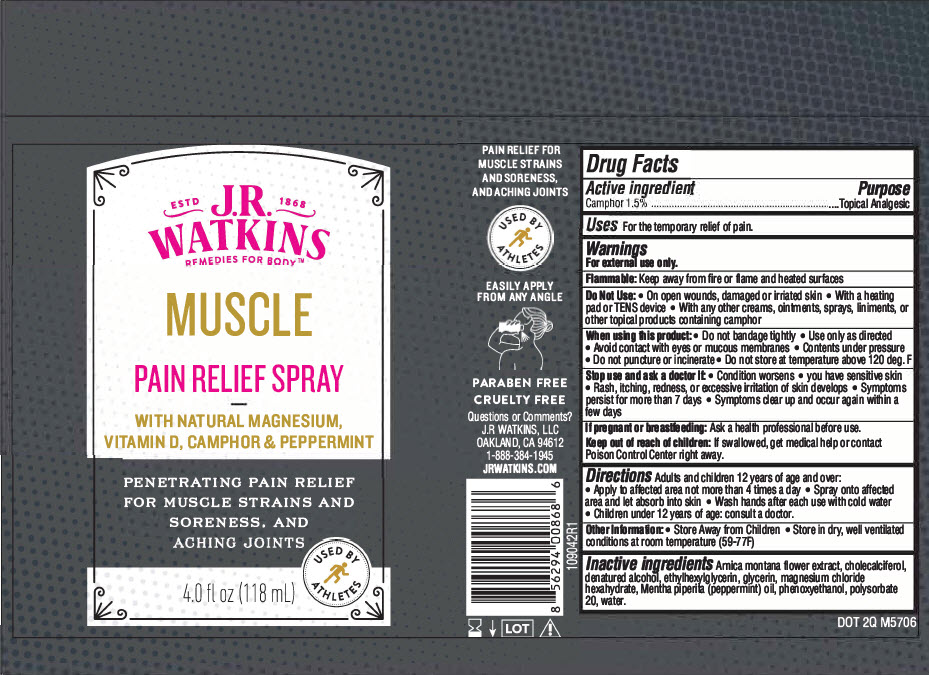 DRUG LABEL: Pain Relief
NDC: 72342-180 | Form: AEROSOL, SPRAY
Manufacturer: J.R. Watkins, LLC.
Category: otc | Type: HUMAN OTC DRUG LABEL
Date: 20240320

ACTIVE INGREDIENTS: CAMPHOR (NATURAL) 1.5 g/100 mL
INACTIVE INGREDIENTS: ARNICA MONTANA FLOWER; CHOLECALCIFEROL; ALCOHOL; ETHYLHEXYLGLYCERIN; GLYCERIN; MAGNESIUM CHLORIDE; PEPPERMINT OIL; PHENOXYETHANOL; POLYSORBATE 20; WATER

Pain Relief Spray
Muscle

Drug Facts

Active ingredient

Camphor 1.5%

Purpose

Topical Analgesic

Uses

For the temporary relief of pain.

Warnings

For external use only.

Flammable:Keep away from fire or flame and heated surfaces

Do not use

- On open wounds, damaged or irriated skin
- With a heating pad or TENS device
- With any other creams, ointments, sprays, liniments, or other topical products containing camphor

When using this product

- Do not bandage tightly
- Use only as directed
- Avoid contact with eyes or mucous membranes
- Contents under pressure
- Do not puncture or incinerate
- Do not store at temperature above 120 deg. F

Stop use and ask a doctor if

- Condition worsens
- you have sensitive skin
- Rash, itching, redness, or excessive irritation of skin develops
- Symptoms persist for more than 7 days
- Symptoms clear up and occur again within a few days

If pregnant or breastfeeding

Ask a health professional before use.

Keep out of reach of children:If swallowed, get medical help or contact Poison Control Center right away.

Directions

- Adults and children 12 years of age and over:
  - Apply to affected area not more than 4 times a day
  - Spray onto affected area and let absorb into skin
  - Wash hands after each use with cold water
- Children under 12 years of age: consult a doctor.

Other Information

- Store Away from Children
- Store in dry, well ventilated conditions at room temperature (59-77F)

Inactive ingredients

Arnica montana flower extract, cholecalciferol, denatured alcohol, ethylhexylglycerin, glycerin, magnesium chloride hexahydrate, Mentha piperita (peppermint) oil, phenoxyethanol, polysorbate 20, water.

Questions or Comments?

J.R WATKINS, LLC
OAKLAND, CA 94612
1-888-384-1945
JRWATKINS.COM

PRINCIPAL DISPLAY PANEL - 118 mL Bottle Label

ESTD 1868
J.R.
WATKINS
REMEDIES FOR BODY™

MUSCLE

PAIN RELIEF SPRAY

WITH NATURAL MAGNESIUM,
VITAMIN D, CAMPHOR & PEPPERMINT

PENETRATING PAIN RELIEF
FOR MUSCLE STRAINS AND
SORENESS, AND
ACHING JOINTS

USED BY
ATHLETES

4.0 fl oz (118 mL)